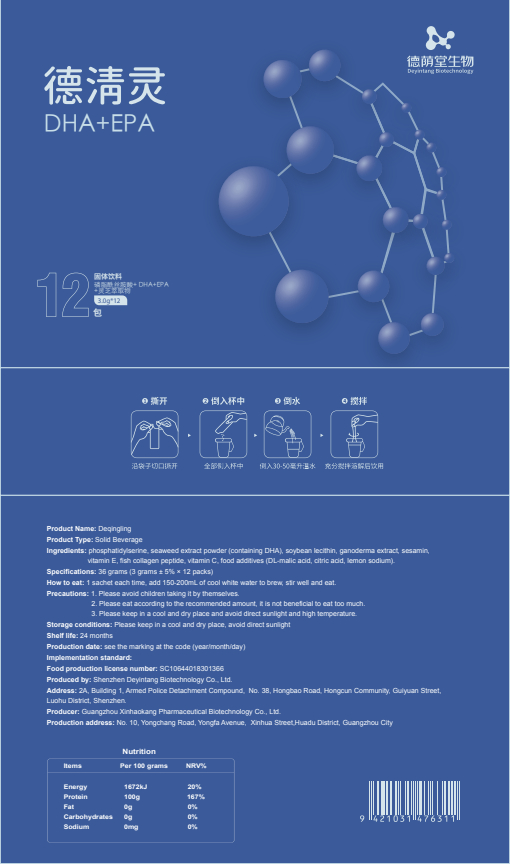 DRUG LABEL: Deqingling
NDC: 82570-017 | Form: POWDER
Manufacturer: Shenzhen Deyintang Biotechnology Co., Ltd.
Category: otc | Type: HUMAN OTC DRUG LABEL
Date: 20220222

ACTIVE INGREDIENTS: SESAMIN 3 g/100 g; .ALPHA.-TOCOPHEROL 2 g/100 g; COLLAGEN, SOLUBLE, FISH SKIN 35 g/100 g; PHOSPHATIDYL SERINE 2 g/100 g; LECITHIN, SOYBEAN 40 g/100 g; ASCORBIC ACID 2 g/100 g; NORI 2 g/100 g; REISHI 3 g/100 g
INACTIVE INGREDIENTS: BLUEBERRY; CITRIC ACID MONOHYDRATE; SODIUM CITRATE; MALIC ACID

ACTIVE INGREDIENT

phosphatidylserine, seaweed extract powder (containing DHA), soybean lecithin, ganoderma extract, sesamin
vitamin E, fish collagen peptide,vitamin C

INACTIVE INGREDIENT

DL-malic acid, citric acid, lemon sodium

PURPOSE

health care

Please avoid children taking it by themselves.

How to eat

1 sachet each time, add 150-200mL of cool white water to brew, stir well and eat.

INDICATIONS AND USAGE

Please eat according to the recommended amount, it is not beneficial to eat too much.

Storage conditions

Please keep in a cool and dry place, avoid direct sunlight

WARNINGS

1.Please avoid children taking it by themselves.
2.Please eat according to the recommended amount, it is not beneficial to eat too much.
3.Please keep in a cool and dry place and avoid direct sunlight and high temperature.